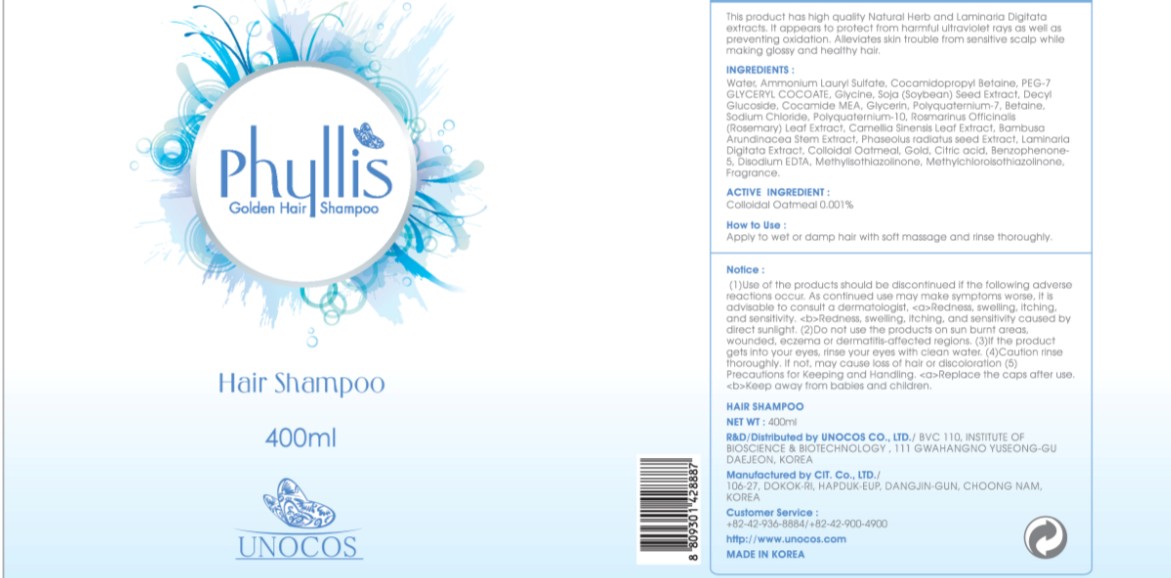 DRUG LABEL: PHYLLIS GOLDEN
NDC: 52841-010 | Form: SHAMPOO
Manufacturer: UNOCOS CO., LTD.
Category: otc | Type: HUMAN OTC DRUG LABEL
Date: 20110121

ACTIVE INGREDIENTS: OATMEAL 0.004 mL/400 mL
INACTIVE INGREDIENTS: WATER; AMMONIUM LAURYL SULFATE; COCAMIDOPROPYL BETAINE; GLYCINE; GOLD; CITRIC ACID MONOHYDRATE; EDETATE DISODIUM; METHYLISOTHIAZOLINONE

Drug Facts

Active Ingredient: OATMEAL

Inactive Ingredients:

WATER, AMMONIUM LAURYL SULFATE, COCAMIDOPROPYL BETAINE, PEG-7 GLYCERYL COCOATE, GLYCINE, SOJA (SOYBEAN) SEED EXTRACT, DECYL SODIUM CHLORIDE,
POLYQUATERNIUM-10, ROSMARINUS OFFICINALIS (ROSEMARY) LEAF EXTRACT, CAMELLIA SINENSIS LEAF EXTRACT, BAMBUSA ARUNDINACEA STEM EXTRACT,
PHASEOLUS RADIATUS SEED EXTRACT, LAMINARIA DIGITATA EXTRACT, GOLD, CITRIC ACID, BENZOPHENONE-5, DISODIUM EDTA, METHYLISOTHIAZOLINONE,
METHYLCHLOROISOTHIAZOLINONE, FRAGRANCE

Purpose:
It appears to protect from harmful ultraviolet rays as well as preventing oxidation.
Alleviates skin trouble from sensitive scalp while making glossy healthy hair.

WARNINGS:
Use of the products should be discontinued if the following adverse reactions occur. As continued use may make symptoms worse, it is advisable to consult a dermatologist, Redness, swelling, itching, and sensitivity.
Redness, swelling, itching, and sensitivity caused by direct sunlight.
Do not use the products on sun burnt areas, wounded, eczema or dermatitis-affected regions.
If the product gets into your eyes, rinse your eyes with clean water.
Caution rinse thoroughly. If not, may cause loss of hair or discoloration

Keep out of reach of children:

Replace the caps after use.

Keep away from babies and children.

INDICATIONS AND USAGE

How to Use:

Apply to wet or damp hair with soft massage and rinse thoroughly.

Dosage and administration:

Apply to wet or damp hair with soft massage and rinse thoroughly.